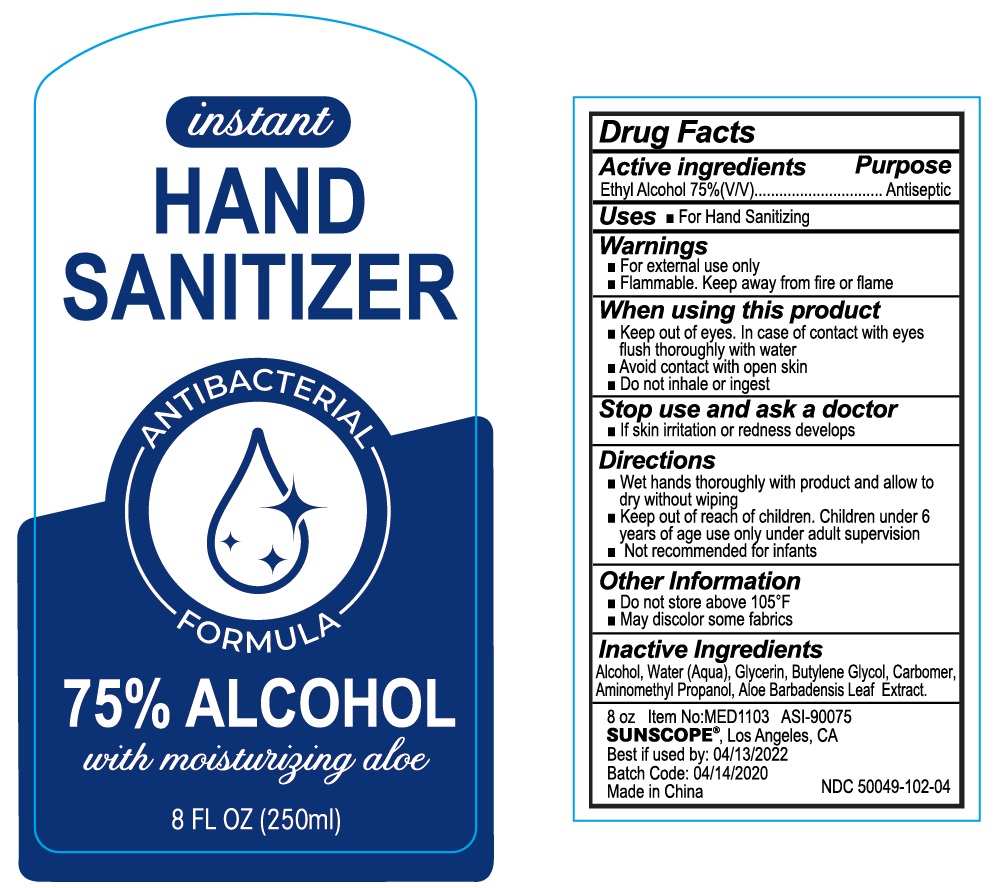 DRUG LABEL: hand sanitizer
NDC: 50049-102 | Form: GEL
Manufacturer: QUANZHOU BESTHOPE HOUSEHOLD PRODUCTS CO.,LTD.
Category: otc | Type: HUMAN OTC DRUG LABEL
Date: 20200420

ACTIVE INGREDIENTS: ALCOHOL 75 mL/100 mL
INACTIVE INGREDIENTS: WATER; GLYCERIN; ALOE VERA LEAF; AMINOMETHYL PROPANEDIOL; CARBOMER 934; BUTYLENE GLYCOL

50049-102 Hand Sanitizer

Active Ingredient

Ethyl Alcohol 75%

Purpose

Antiseptic

Use

For hand Sanitizing

WARNINGS

■For external use only
n Flammable. Keep away from fire or flame
When using this product
n Keep out of eyes. In case of contact with eyes
flush thoroughly with water
■Avoid contact with open skin
1 Do not inhale or ingest
Stop use and ask a doctor
n If skin iritation or redness develops

■Keep out of reach of children. Children under 6
years of age use only under adult supervision
■Not recommended for infants

Directions

■Wet hands thoroughly with product and alow to dry
without wiping

Inactive ingredients

Aloohol, Water(Aqua), Glycenin, Butylene Glycol, Carbomer,Aminomethyl Propanol, Aloe Barbadensis Leaf Extract